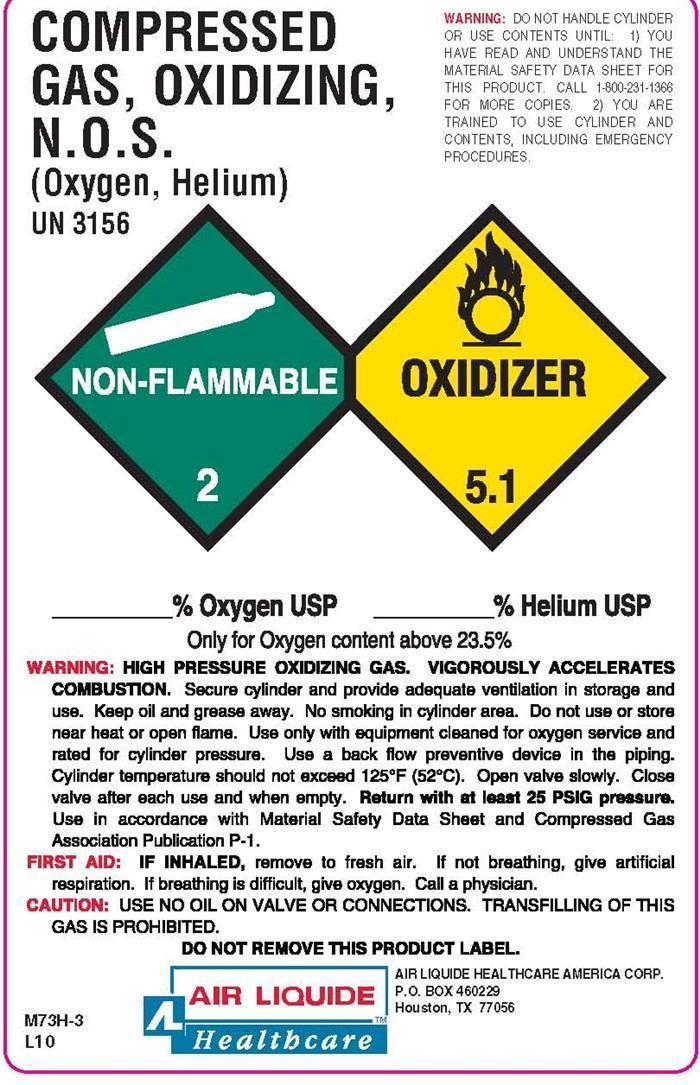 DRUG LABEL: COMPRESSED GAS, OXIDIZING, N.O.S.
NDC: 64735-070 | Form: GAS
Manufacturer: Air Liquide Healthcare America Corporation
Category: prescription | Type: HUMAN PRESCRIPTION DRUG LABEL
Date: 20140825

ACTIVE INGREDIENTS: OXYGEN 40 L/100 L
INACTIVE INGREDIENTS: HELIUM

Compressed Gas, Oxidizing, N.O.S. (OXYGEN, HELIUM) Label

WARNING: DO NOT HANDLE CYLINDER OR USE CONTENTS UNTIL: 1) YOU HAVE READ AND UNDERSTAND THE MATERIAL SAFETY DATA SHEET FOR THIS PRODUCT. CALL 1-800-231-1366 FOR MORE COPIES. 2) YOU ARE TRAINED TO USE CYLINDER AND CONTENTS, INCLUDING EMERGENCY PROCEDURES.

COMPRESSED GAS, OXIDIZING, N.O.S. (OXYGEN, HELIUM) UN 3156

NON-FLAMMABLE 2 OXIDIZER 5.1

_________ % Oxygen USP ________ % Helium USP

Only for Oxygen contents above 23.5%

WARNING: HIGH PRESSURE, OXIDIZING GAS, VIGOROUSLY ACCELERATES COMBUSTION. Secure cylinder and provide adequate ventilation in storage and use. Keep oil and grease away. No smoking in cylinder area. Do not use or store near heat or open flame. Use only with equipment cleaned for oxygen service and rated for cylinder pressure. Use a back flow preventive device in the piping. Cylinder temperatures should not exceed 125°F (52°C). Open valve slowly. Close valve after each use and when empty. Return with at least 25 PSIG pressure. Use in accordance with Material Safety Data Sheet and Compressed Gas Association Publication P-1.
FIRST AID: IF INHALED, remove to fresh air. If not breathing, give artificial respiration. If breathing is difficult, give oxygen. Call a physician.
CAUTION: USE NO OIL ON VALVE OR CONNECTIONS. TRANSFILLING OF THIS GAS IS PROHIBITED.
DO NOT REMOVE THIS PRODUCT LABEL.

AIR LIQUIDE HEALTHCARE AMERICA CORP.
P. O. BOX 460229
Houston, TX 77056

M73H-3 L10